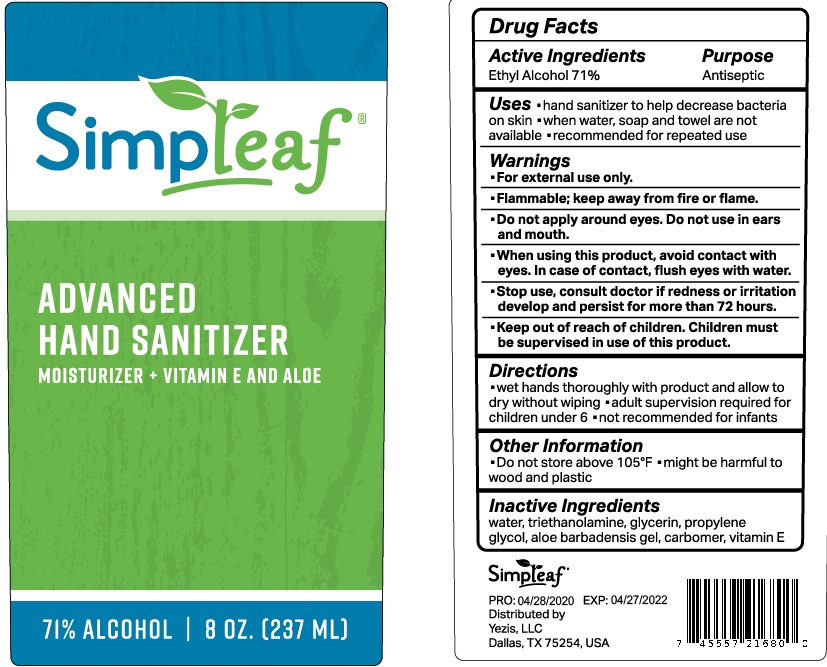 DRUG LABEL: Simpleaf Advanced Hand Sanitizer Moisturizer and Vitamin E and Aloe
NDC: 75780-012 | Form: GEL
Manufacturer: NINGBO MEINEKE Biotech Technology Co., Ltd.
Category: otc | Type: HUMAN OTC DRUG LABEL
Date: 20200522

ACTIVE INGREDIENTS: alcohol 71 mL/100 mL
INACTIVE INGREDIENTS: WATER; PROPYLENE GLYCOL; ALOE VERA LEAF; CARBOMER 934; GLYCERIN; TROLAMINE

Drug facts

Active ingredient(s) Purpose

Alcohol 71% ............... Antiseptic

PURPOSE

- Hand sanitizer to help decrease bacteria on the skin.
- When water, soap and towel are not available.
- Recommendd for repeated use.

KEEP OUT OF REACH OF CHILDREN

Children must be supervised in use of this product.

INDICATIONS AND USAGE

- Wet hands thoroughly with product and allow to dry without wiping
- adult supervision required for children under 6
- Not recommended for infants.

WARNINGS

For external use only.
Flammable. Keep away from fire or flame.

Do not apply around eyes. Do not use in ears and mouth.

When using this product, avoid contact with eyes. In case of contact, flush eyes with water.

Stop using, consult doctor if redness or irritation develop and persist for more than 72 hours.

Other information:

- Do not Store above 105℉
- might be harmful to wood and plastic

INACTIVE INGREDIENT

Water, Triethanolamine, Glycerin, Propylene glycol, Aloe Barbadensis gel, carbomer, vitamin E